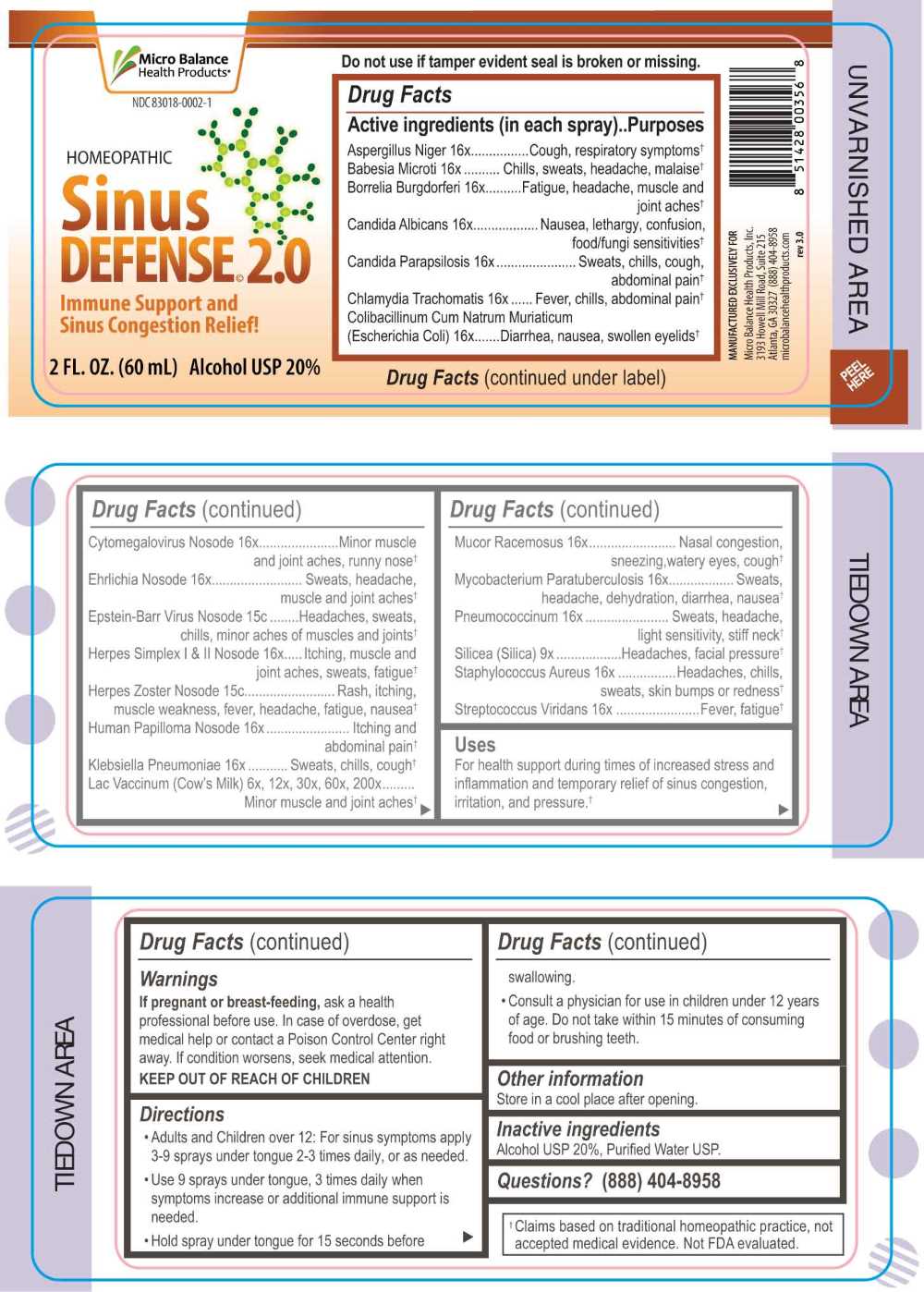 DRUG LABEL: Sinus Defense
NDC: 83018-0002 | Form: SPRAY
Manufacturer: Micro Balance Health Products LLC
Category: homeopathic | Type: HUMAN OTC DRUG LABEL
Date: 20250407

ACTIVE INGREDIENTS: COW MILK 6 [hp_X]/1 mL; SILICON DIOXIDE 9 [hp_X]/1 mL; ASPERGILLUS NIGER VAR. NIGER 16 [hp_X]/1 mL; BABESIA MICROTI 16 [hp_X]/1 mL; BORRELIA BURGDORFERI 16 [hp_X]/1 mL; CANDIDA ALBICANS 16 [hp_X]/1 mL; CANDIDA PARAPSILOSIS 16 [hp_X]/1 mL; CHLAMYDIA TRACHOMATIS 16 [hp_X]/1 mL; ESCHERICHIA COLI 16 [hp_X]/1 mL; HUMAN HERPESVIRUS 5 16 [hp_X]/1 mL; EHRLICHIA CANIS 16 [hp_X]/1 mL; HUMAN HERPESVIRUS 1 16 [hp_X]/1 mL; HUMAN HERPESVIRUS 2 16 [hp_X]/1 mL; HUMAN PAPILLOMAVIRUS 16 [hp_X]/1 mL; KLEBSIELLA PNEUMONIAE 16 [hp_X]/1 mL; MUCOR RACEMOSUS 16 [hp_X]/1 mL; MYCOBACTERIUM AVIUM SUBSP. PARATUBERCULOSIS 16 [hp_X]/1 mL; Streptococcus pneumoniae 16 [hp_X]/1 mL; STAPHYLOCOCCUS AUREUS 16 [hp_X]/1 mL; STREPTOCOCCUS VIRIDANS GROUP 16 [hp_X]/1 mL; HUMAN HERPESVIRUS 4 15 [hp_C]/1 mL; HUMAN HERPESVIRUS 3 15 [hp_C]/1 mL
INACTIVE INGREDIENTS: WATER; ALCOHOL

DRUG FACTS:

ACTIVE INGREDIENTS:

Aspergillus Niger 16X, Babesia Microti 16X, Borrelia Burgdorferi 16X, Candida Albicans 16X, Candida Parapsilosis 16X, Chlamydia Trachomatis 16X, Colibacillinum Cum Natrum Muriaticum (Escherichia Coli) 16X, Cytomegalovirus Nosode 16X, Ehrlichia Nosode 16X, Epstein-Barr Virus Nosode 15C, Herpes Simplex I & II Nosode 16X, Herpes Zoster Nosode 15C, Human Papilloma Nosode 16X, Klebsiella Pneumoniae 16X, Lac Vaccinum (Cow’s Milk) 6X, 12X, 30X, 60X, 200X, Mucor Racemosus 16X, Mycobacterium Paratuberculosis 16X, Pneumoccoccinum 16X, Silicea (Silica) 9X, Staphylococcus Aureus 16X, Streptococcus Viridans 16X.

PURPOSE:

Aspergillus Niger – Cough, respiratory symptoms,† Babesia Microti – Chills, sweats, headache, malaise,† Borrelia Burgdorferi – Fatigue, headache, muscle and joint aches,† Candida Albicans – Nausea, lethargy, confusion, food/fungi sensitivities,† Candida Parapsilosis – Sweats, chills, cough, abdominal pain,† Chlamydia Trachomatis – Fever, chills, abdominal pain,† Colibacillinum Cum Natrum Muriaticum (Escherichia Coli) – Diarrhea, nausea, swollen eyelids,† Cytomegalovirus Nosode – Minor muscle and joint aches, runny nose,† Ehrlichia Nosode - Sweats, headache, muscle and joint aches,† Epstein-Barr Virus Nosode – Headaches, sweats, chills, minor aches of muscles and joints,† Herpes Simplex I & II Nosode – Itching, muscle and joint aches, sweats, fatigue,† Herpes Zoster Nosode – Rash, itching, muscle weakness, fever, headache, fatigue, nausea,† Human Papilloma Nosode – Itching and abdominal pain,† Klebsiella Pneumoniae – Sweats, chills, cough,† Lac Vaccinum (Cow’s Milk) – Minor muscle and joint aches,† Mucor Racemosus – Nasal congestion, sneezing, watery eyes, cough,† Mycobacterium Paratuberculosis – Sweats, headache, dehydration, diarrhea, nausea,† Pneumoccoccinum – Sweats, headache, light sensitivity, stiff neck,† Silicea (Silica) – Headaches, facial pressure,† Staphylococcus Aureus – Headaches, chills, sweats, skin bumps or redness,† Streptococcus Viridans – Fever, fatigue†

†Claims based on traditional homeopathic practice, not accepted medical evidence. Not FDA evaluated.

USES:

For health support during times of increased stress and inflammation and temporary relief of sinus congestion, irritation, and pressure.†

†Claims based on traditional homeopathic practice, not accepted medical evidence. Not FDA evaluated.

WARNINGS:

If pregnant or breast-feeding, ask a health professional before use.

In case of overdose, get medical help or contact a Poison Control Center right away.

If condition worsen, seek medical attention.

KEEP OUT OF REACH OF CHILDREN

Do not use if tamper evident seal is broken or missing.

Store in a cool place after opening

KEEP OUT OF REACH OF CHILDREN:

In case of overdose, get medical help or contact a Poison Control Center right away.

DIRECTIONS:

• Adults and Children over 12: For sinus symptoms apply 3-9 sprays under tongue 2-3 times daily, or as needed.

• Use 9 sprays under tongue, 3 times daily when symptoms increase or additional immune support is needed.

• Hold spray under tongue for 15 seconds before swallowing.

Consult a physician for use in children under 12 years of age. Do not take within 15 minutes of consuming food or brushing teeth.

INACTIVE INGREDIENTS:

Alcohol USP 20%, Purified Water USP.

QUESTIONS:

MANUFACTURED EXCLUSIVELY FOR

Micro Balance Health Products, Inc.

3193 Howell Mill Road, Suite 215

Atlanta, GA 30327 (888) 404-8958

www.microbalancehealthproducts.com

PACKAGE LABEL DISPLAY:

Micro Balance

Health Products

NDC 83018-0002-1

HOMEOPATHIC

SINUS

DEFENSE 2.0

Immune Support and

Sinus Congestion Relief!

2FL. OZ. (60 ml)